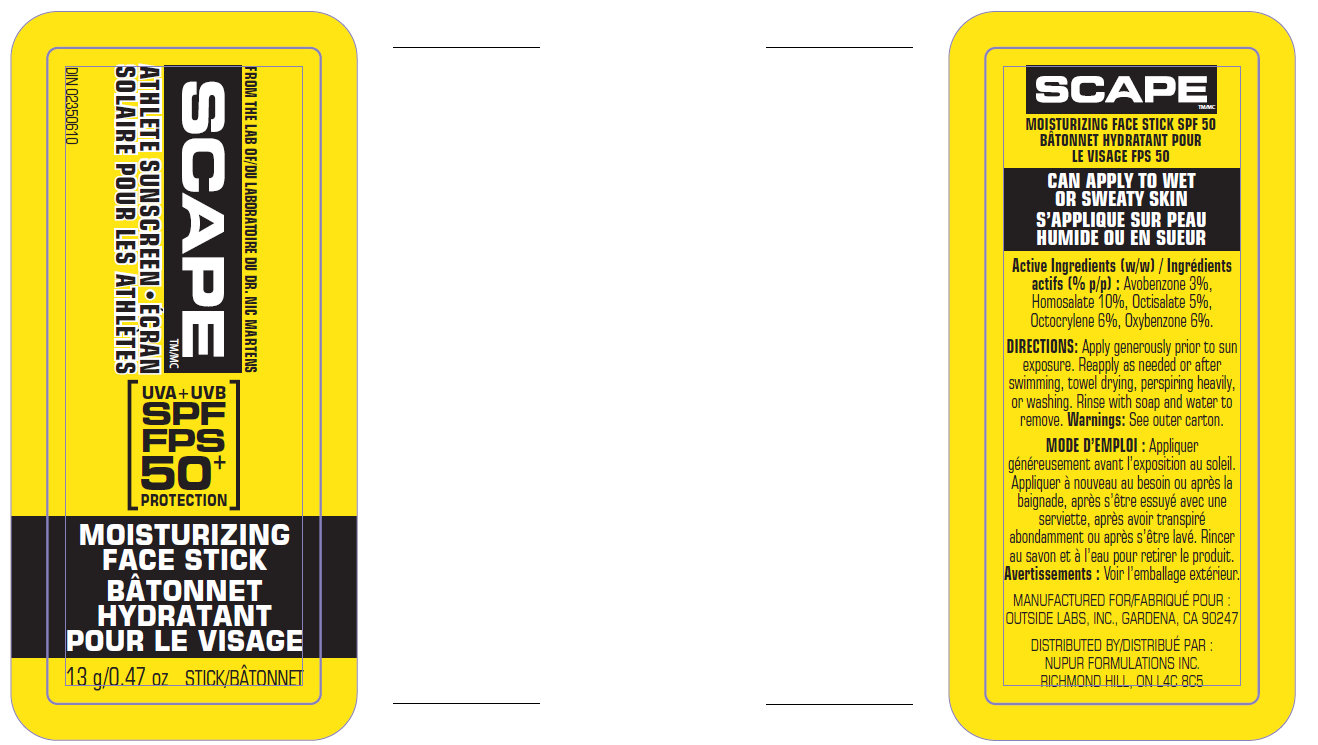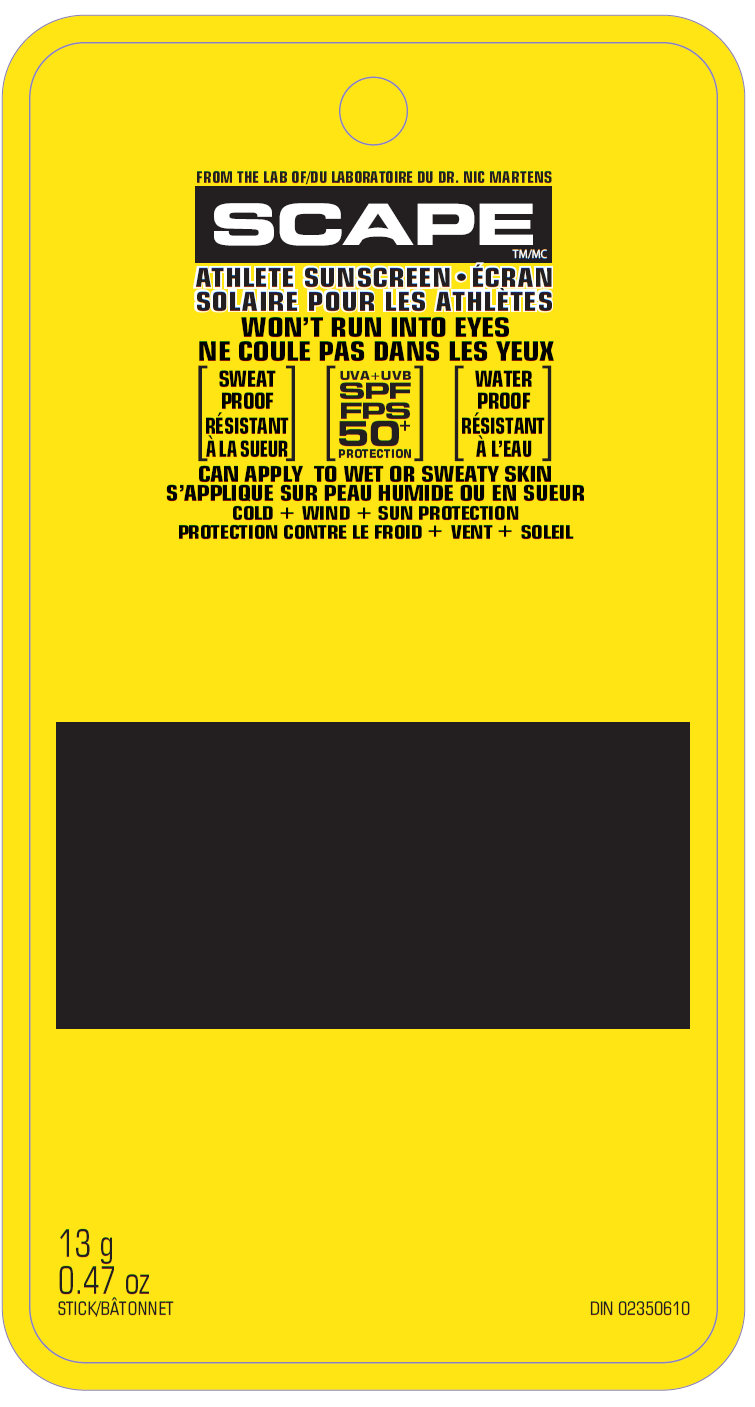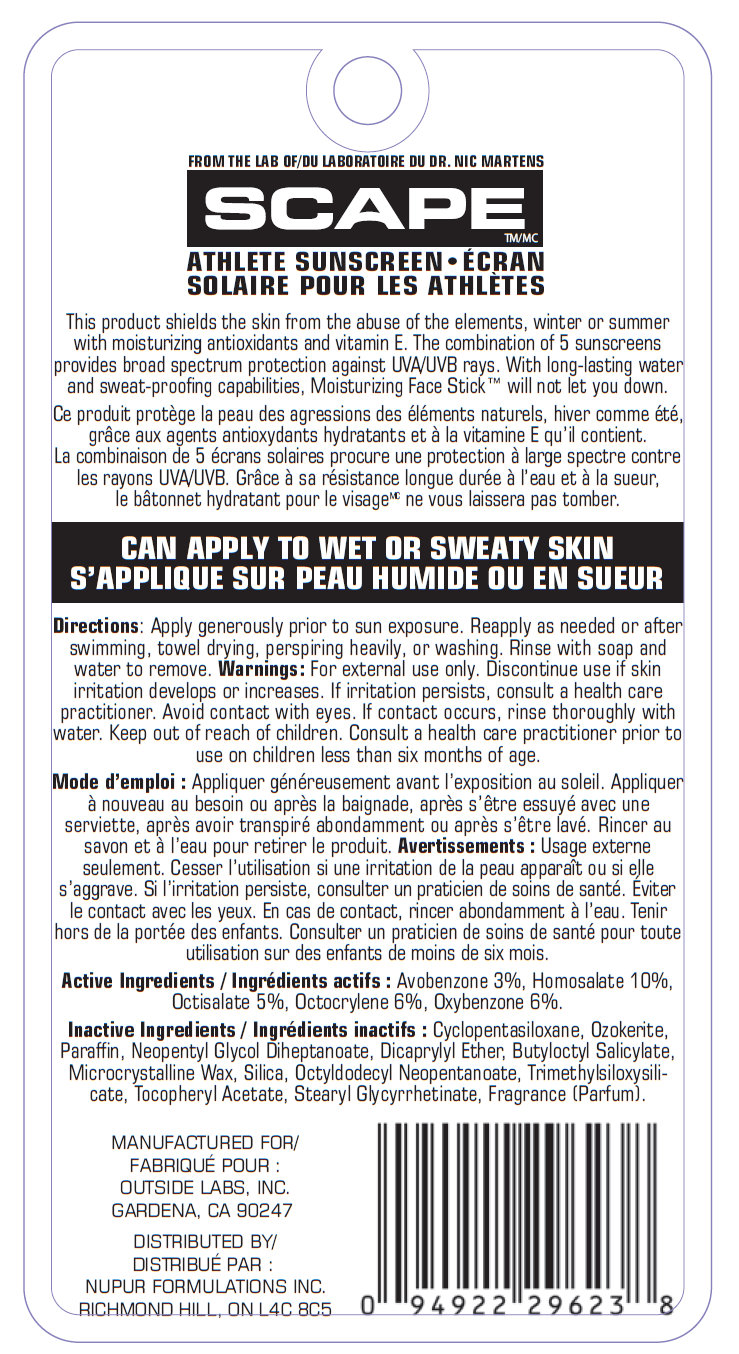 DRUG LABEL: Scape SPF 50 Moisturizing Face
NDC: 76174-130 | Form: STICK
Manufacturer: Nupur Formulations Inc
Category: otc | Type: HUMAN OTC DRUG LABEL
Date: 20110422

ACTIVE INGREDIENTS: AVOBENZONE 3 g/100 g; HOMOSALATE 10 g/100 g; OCTISALATE 5 g/100 g; OCTOCRYLENE 6 g/100 g; OXYBENZONE 6 g/100 g
INACTIVE INGREDIENTS: CYCLOMETHICONE 5; CERESIN; PARAFFIN; NEOPENTYL GLYCOL DIHEPTANOATE; DICAPRYLYL ETHER; BUTYLOCTYL SALICYLATE; MICROCRYSTALLINE WAX; SILICON DIOXIDE; OCTYLDODECYL NEOPENTANOATE; ALPHA-TOCOPHEROL ACETATE

Scape SPF 50+ Moisturizing Face Stick

FROM THE LAB OF DR. NIC MARTENS

SCAPE

ATHLETE SUNSCREEN

This product shields the skin from the abuse of the elements, winter or summer with moisturizing antioxidants and vitamin E. The combination of 5 sunscreens provides broad spectrum protection against UVA/UVB rays. With long-lasting water and sweat-proofing capabilities, Moisturizing Face Stick will not let you down

DOSAGE AND ADMINISTRATION

Directions: Apply generously prior to sun exposure. Reapply as needed or after swimming, towel drying, perspiring heavily, or washing. Rinse with soap and water to remove.

WARNINGS

Warnings: For external use only. Discontinue use if skin irritation develops or increases. If irritation persists, consult a health care practitioner. Avoid contact with eyes. If contact occurs, rinse thoroughly with water. Keep out of reach of children. Consult a health care practitioner prior to use on children less than six months of age.

Active Ingredients:

Avobenzone 3%, Homosalate 15%, Octocrylene 6%, Oxybenzone 6%

Inactive Ingredients:

Cyclopentasiloxane, Ozokerite, Paraffin, Neopentyl Glycol Diheptanoate, Dicaprylyl Ether, Butyloctyl Salicylate, Microcrystalline Wax, Silica, Octyldodecyl Neopentanoate, Trimethylsiloxysilicate, Tocopheryl Acetate, Stearyl Glycyrrhetinate, Fragrance (Parfum)

MANUFACTURED FOR/

Outside Labs, Inc.

GARDENA CA 90247

DISTRIBUTED BY/

SCAPElabs.com

NUPUR FORMULATIONS INC
RICHMOND HILL ON L40 8C5

PACKAGE LABEL

FROM THE LAB OF DR. NIC MARTENS

SCAPE

ATHLETE SUNSCREEN

UVA + UVB

SPF 50+ PROTECTION

WON'T RUN INTO EYES

WATERPROOF AND SWEATPROOF

CAN APPLY TO WET OR SWEATY SKIN

COLD + WIND + SUN PROTECTION

13g

0.47 oz

Stick